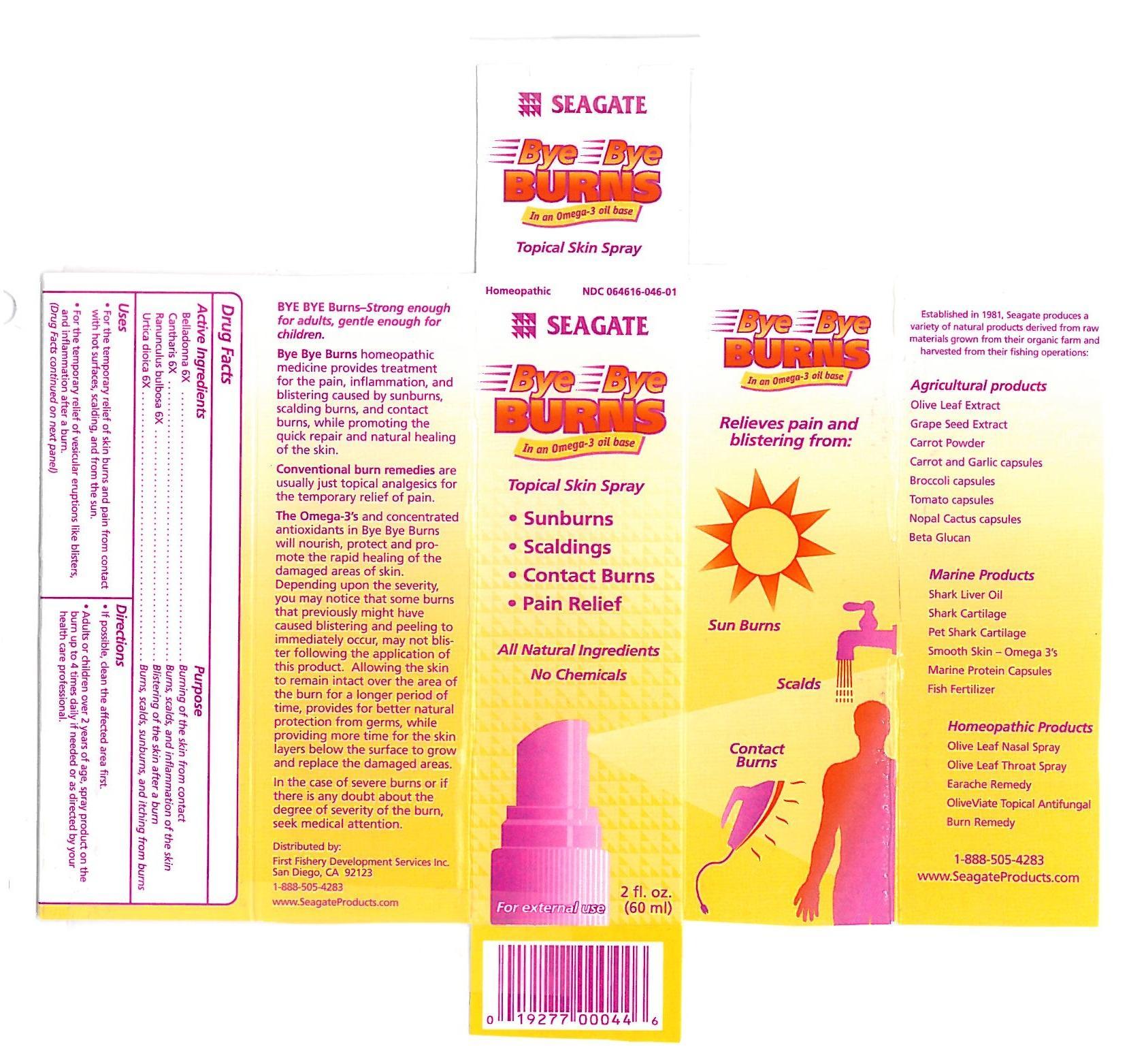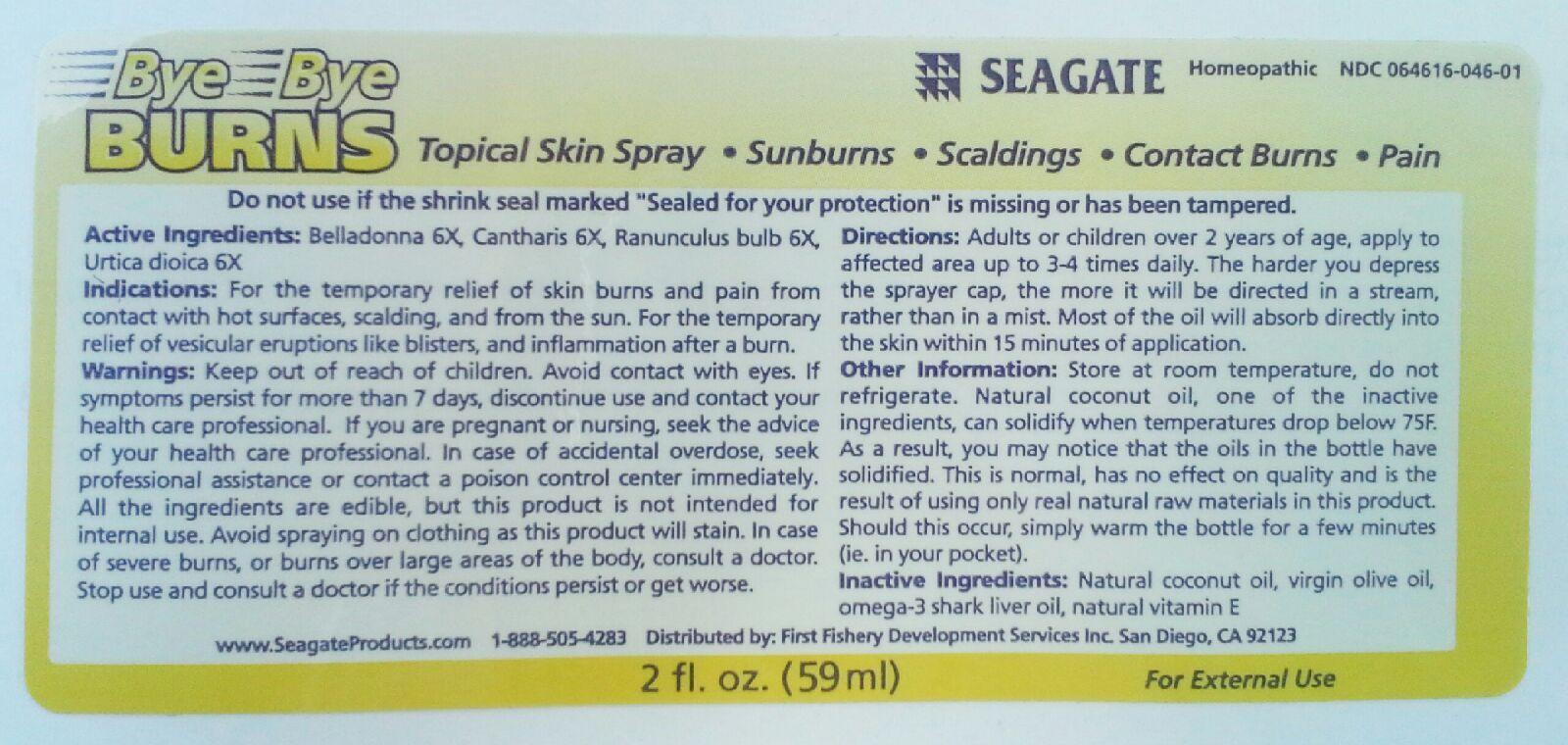 DRUG LABEL: Bye Bye Burns
NDC: 64616-046 | Form: SPRAY
Manufacturer: Vitality Works, Inc
Category: homeopathic | Type: HUMAN OTC DRUG LABEL
Date: 20171204

ACTIVE INGREDIENTS: ATROPA BELLADONNA 6 [hp_X]/1 mL; LYTTA VESICATORIA 6 [hp_X]/1 mL; RANUNCULUS BULBOSUS 6 [hp_X]/1 mL; URTICA DIOICA 6 [hp_X]/1 mL
INACTIVE INGREDIENTS: COCONUT OIL; OLIVE OIL; SHARK LIVER OIL; ALPHA-TOCOPHEROL

Bye Bye Burns

Bye Bye Burns

Belladonna 6X

Cantharis 6X

Ranunculus bulbosa 6X

Urtica dioica 6X

Bye Bye Burns

Natural coconut oil, virgin olive oil, omega-3 shark liver oil, natural vitamin E.

Bye Bye Burns

Avoid contact with eyes. If symptoms persist for more than 7 days, discontinue use and contact your health care professional. In case of accidental overdose seek professional assistance or contact a poison control center immediately. All the ingredients are edible, but this product is not intended for internal use. Avoid spraying on clothing as the product will stain. In case of severe burns, or burns over large areas of the body, consult a doctor. Stop use and consult a doctor if the conditions persist or get worse.

Bye Bye Burns

Keep out of reach of children.

Bye Bye Burns

For the temporary relief of skin burns and pain from contact with hot surfaces, scalding, and from the sun. For the temporary reief of vesicular eruptions like blisters, and inflammation after a burn.

Bye Bye Burns

Adults or children over 2 years of age, apply to affected area up to 3-4 times daily. The harder you depress the sprayer cap, the more it will be directed in a stream rather than in a mist. Most of the oil will absorb directly into the skin within 15 minutes of application.

Bye Bye Burns

Belladonna - burning of the skin from contact

Cantharis - burns, scalds, and inflammation of the skin

Ranunculus bulbosa - blistering of the skin after a burn

Urtica dioica - burns, scalds, sunburns and itching from burns.